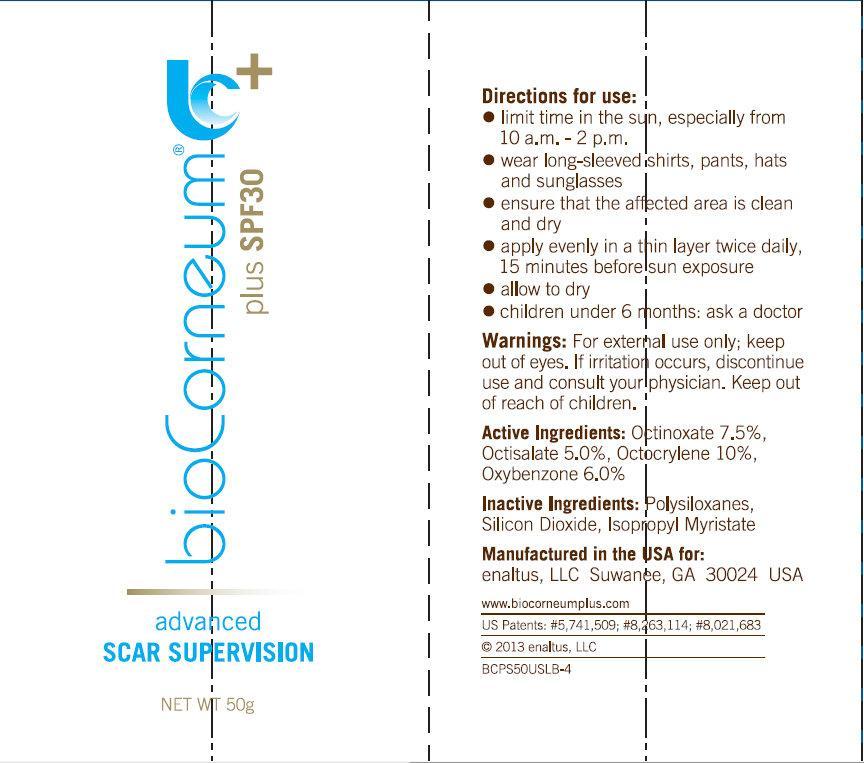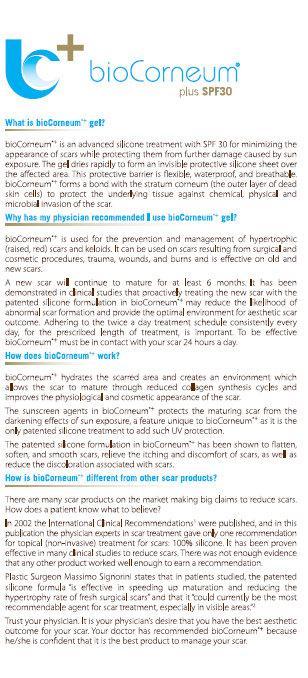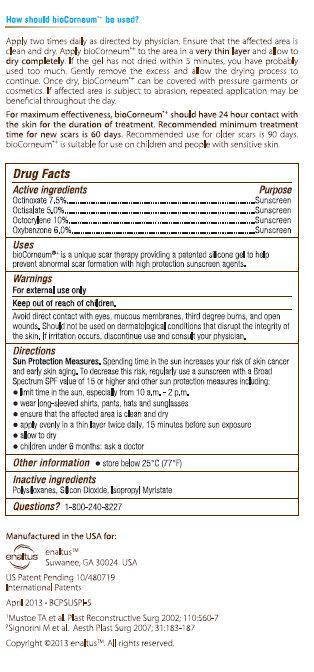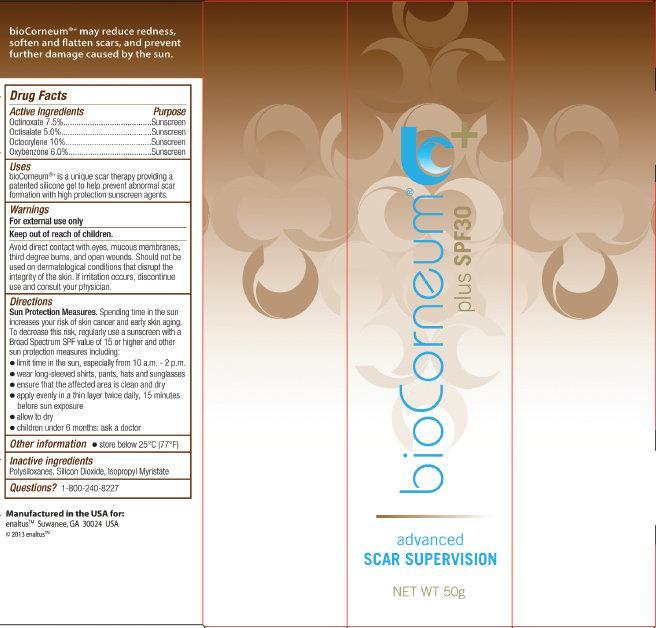 DRUG LABEL: bioCorneum  plus SPF 30 advanced SCAR SUPERVISION
NDC: 43474-001 | Form: GEL
Manufacturer: Enaltus Inc
Category: otc | Type: HUMAN OTC DRUG LABEL
Date: 20140410

ACTIVE INGREDIENTS: OCTINOXATE 7.5 g/100 g; OCTISALATE 5 g/100 g; OCTOCRYLENE 10 g/100 g; OXYBENZONE 6 g/100 g
INACTIVE INGREDIENTS: SILICON DIOXIDE; ISOPROPYL MYRISTATE

bioCorneum + plus SPF 30 advanced SCAR SUPERVISION

Active ingredients

Octinoxate 7.5%
Octisalate 5.0%
Octocrylene 10%
Oxybenzone 6.0%

Purpose

Sunscreen

Uses

bioCorneumis a unique scar therapy providing a patented silicone gel to help prevent abnormal scar formation with high protection sunscreen agents.

Warnings

For external use only

WHEN USING

Avoid direct contact with eyes, mucous membranes, third degree burns, and open wounds.

DO NOT USE

Should not be used on dermatological conditions that disrupt the integrity of the skin.

STOP USE

If irritation occurs, discontinue use and consult your physician.

Directions

Sun Protection Measures. Spending time in the sun increases your risk of skin cancer and early skin aging. To decrease this risk, regularly use a sunscreen with a Broad Spectrum SPF value of 15 or higher and other sun protection measures including:

- limit time in the sun, especially from 10 a.m. - 2 p.m.
- wear long-sleeved shirts, pants, hats and sunglasses
- ensure that the affected area is clean and dry
- apply evenly in a thin layer twice daily, 15 minutes before sun exposure
- allow to dry
- children under 6 months: ask a doctor

Other information

- store below 25oC (77oF)

Inactive ingredients

Polysiloxanes, Silicon Dioxide, Isopropyl Myristate

Questions?

1-800-240-8227

Representative Labeling

bioCorneum + plus SPF 30 advanced SCAR SUPERVISION 50g (43474-001-50)
bioCorneum + plus SPF 30 advanced SCAR SUPERVISION 20g (43474-001-20)
bioCorneum + plus SPF 30 advanced SCAR SUPERVISION 10g (43474-001-10)